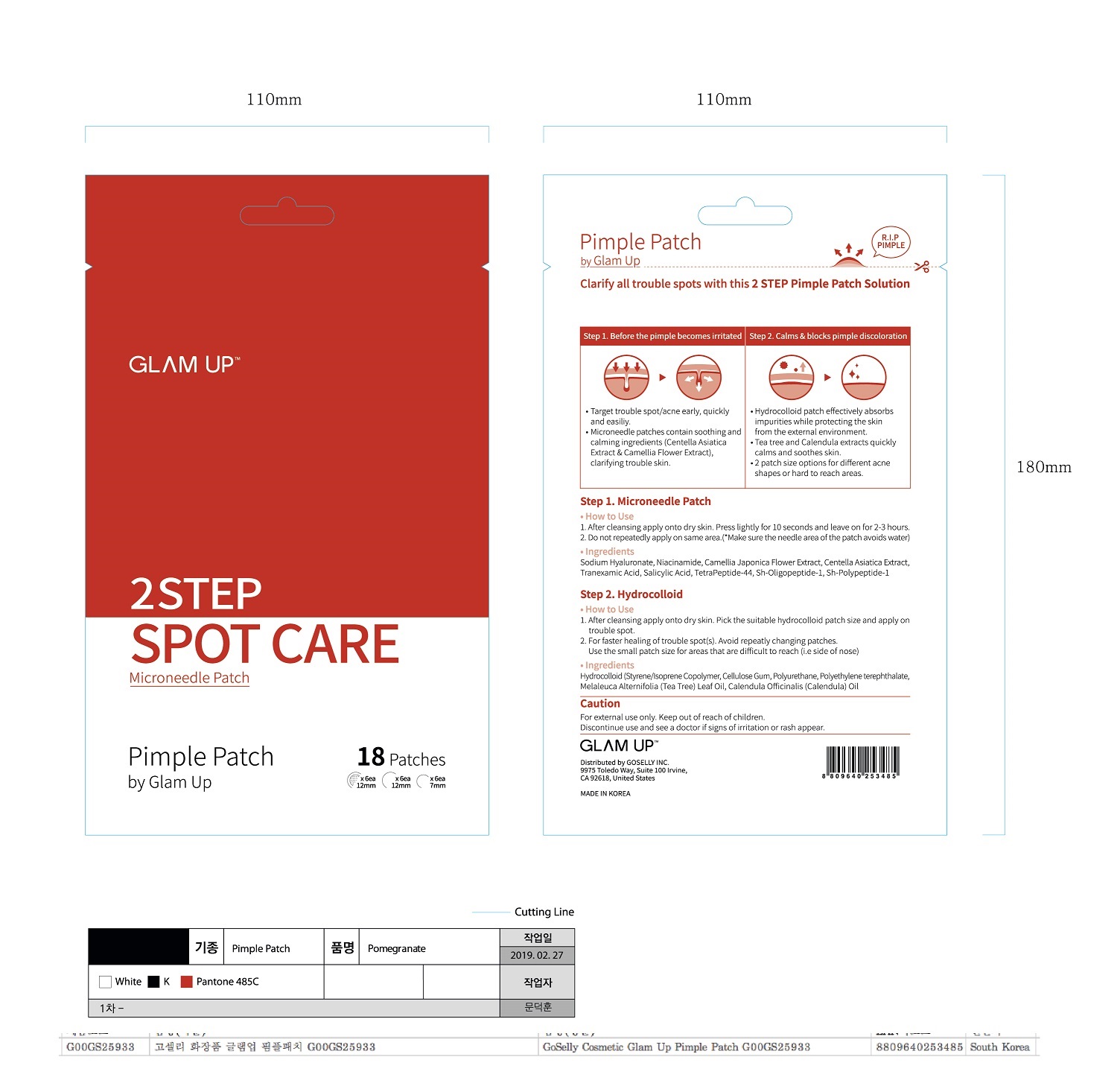 DRUG LABEL: PIMPLEPATCH BY GLAM UP
NDC: 73085-0001 | Form: KIT | Route: TOPICAL
Manufacturer: Spigen Korea Co., Ltd.
Category: otc | Type: HUMAN OTC DRUG LABEL
Date: 20210825

ACTIVE INGREDIENTS: MELALEUCA ALTERNIFOLIA LEAF 1 mg/100 mg; SALICYLIC ACID 0.44 mg/100 mg
INACTIVE INGREDIENTS: SODIUM STARCH GLYCOLATE TYPE A CORN; CALENDULA OFFICINALIS SEED OIL; WATER; BUTYLENE GLYCOL

ACTIVE INGREDIENT

salicylic aid

INACTIVE INGREDIENT

Sodium Hyaluronate, Niacinamide, Sh-Oligopeptide-1, Sh-Polypeptide-1, TetraPeptide-44, Centella Asiatica Extract, Tranexamic Acid, Camellia Japonica Flower Extract, etc

PURPOSE

target trouble spot/acne early, quickly and easily

Keep out of reach of the children

INDICATIONS AND USAGE

step 1. microneedle patch

1. after cleansing apply onto dry skin, press lightly for 10 seconds and leave on for 2~3 hours

2. do not repeatedly apply on same area (make sure the needle area of the patch avoids water)

step 2. hydrocolloid

1. after cleansing apply on to dry skin, pick the suitable hydrocolloid patch size and apply on trouble spot

2. for faster healing of trouble spot(s), avoid repeatly changing patches. use the small patch size for areas that are difficult to reach (i.e., side of nose)

WARNINGS

1. Do not use in the following cases(Eczema and scalp wounds)
2.Side Effects
1)Due to the use of this druf if rash, irritation, itching and symptopms of hypersnesitivity occur dicontinue use and consult your phamacisr or doctor
3.General Precautions
1)If in contact with the eyes, wash out thoroughty with water If the symptoms are servere, seek medical advice immediately
2)This product is for exeternal use only. Do not use for internal use
4.Storage and handling precautions
1)If possible, avoid direct sunlight and store in cool and area of low humidity
2)In order to maintain the quality of the product and avoid misuse
3)Avoid placing the product near fire and store out in reach of children

DOSAGE AND ADMINISTRATION

for external use only